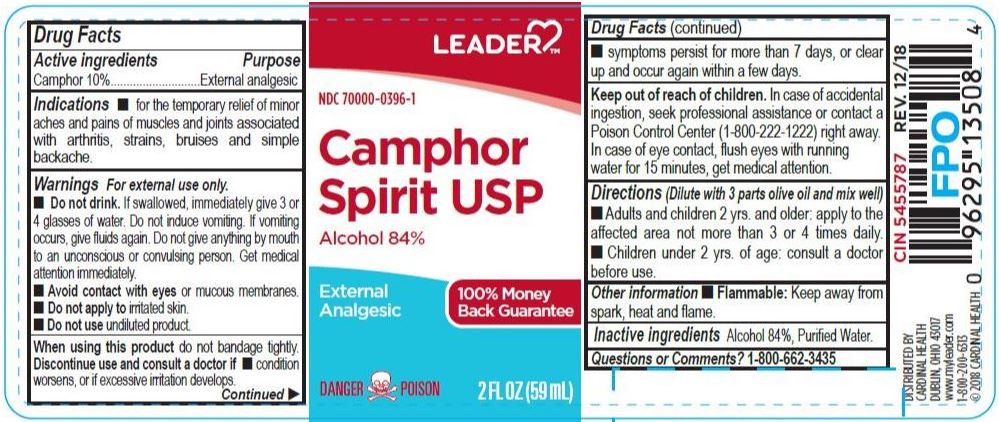 DRUG LABEL: LEADER Camphor Spirit
NDC: 70000-0396 | Form: LIQUID
Manufacturer: Cardinal Health, 110 dba Leader
Category: otc | Type: HUMAN OTC DRUG LABEL
Date: 20231222

ACTIVE INGREDIENTS: CAMPHOR (NATURAL) 100 mg/1 mL
INACTIVE INGREDIENTS: WATER; ALCOHOL

LEADER Camphor Spirit (New NDC)

DOSAGE AND ADMINISTRATION

(Dillute with 3 parts olive oil and mix well)

Adults and children 2 yrs. and older apply to the affected area not more than 3 or 4 times daily.

Children under 2 yrs. of age: consult a doctor before use.

INACTIVE INGREDIENT

Alcohol 84%, Purified Water

KEEP OUT OF REACH OF CHILDREN

In case of accidental ingestion, seek professional assistance or contact a Poison Control Center right away. In case of eye contact, flush eyes with running water for 15 minutes, get medical attention.

PURPOSE

External Analgesic

WARNINGS

For external use only.

Do not drink. If swallowed, immediately give 3 or 4 glasses of water. Do not induce vomiting. If vomiting occurs, give fluids again. Do not give anything by mouth to an unconscious or convulsing person. Get medical attention immediately.

Avoid contact with eyes or mucous membranes.

Do not apply to irritated skin.

INDICATIONS AND USAGE

For the temporary relief of minor aches, muscle and jooint pain associated with artritis, strains, bruises and simple backache

ACTIVE INGREDIENT

Camphor 10%